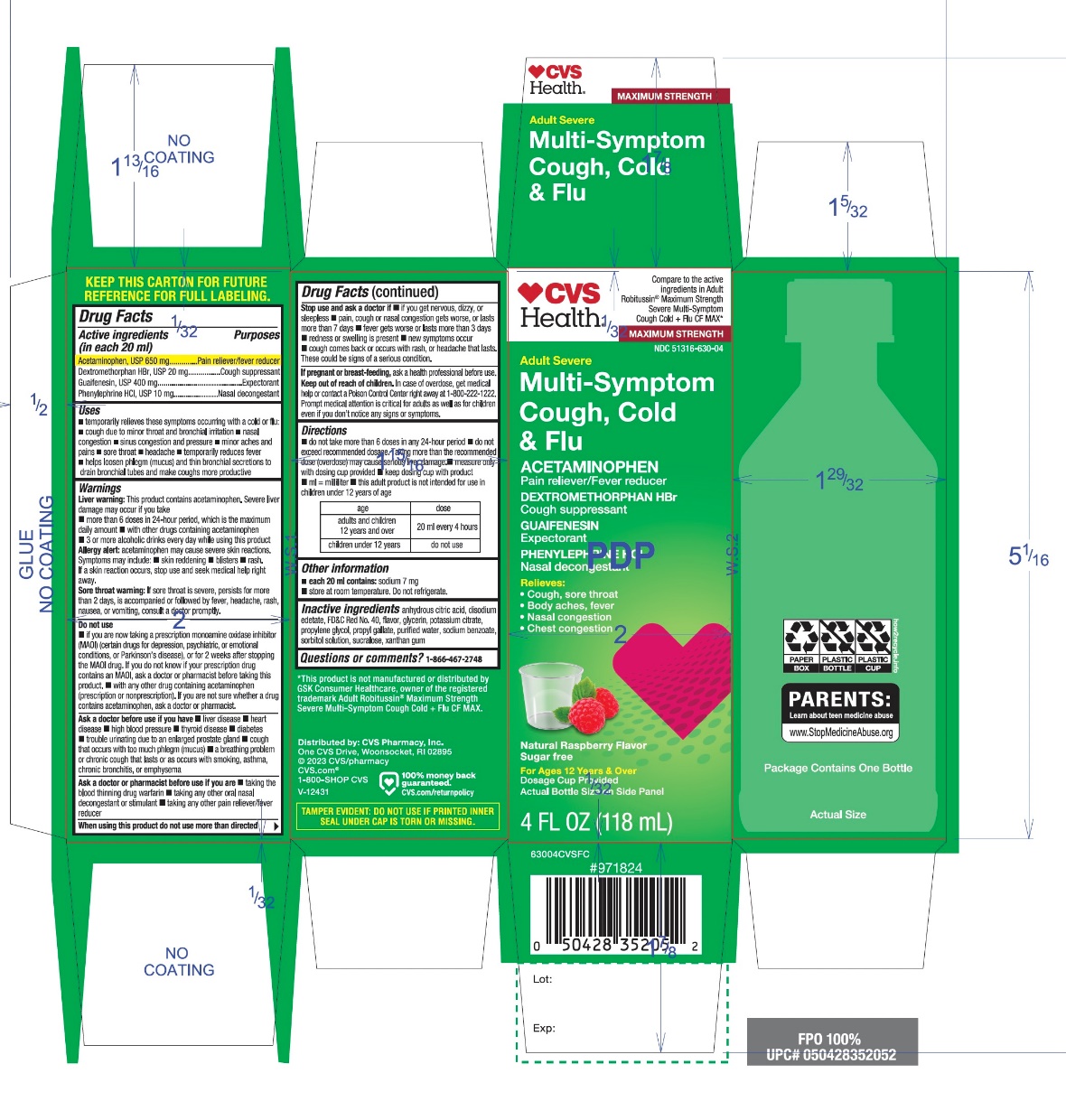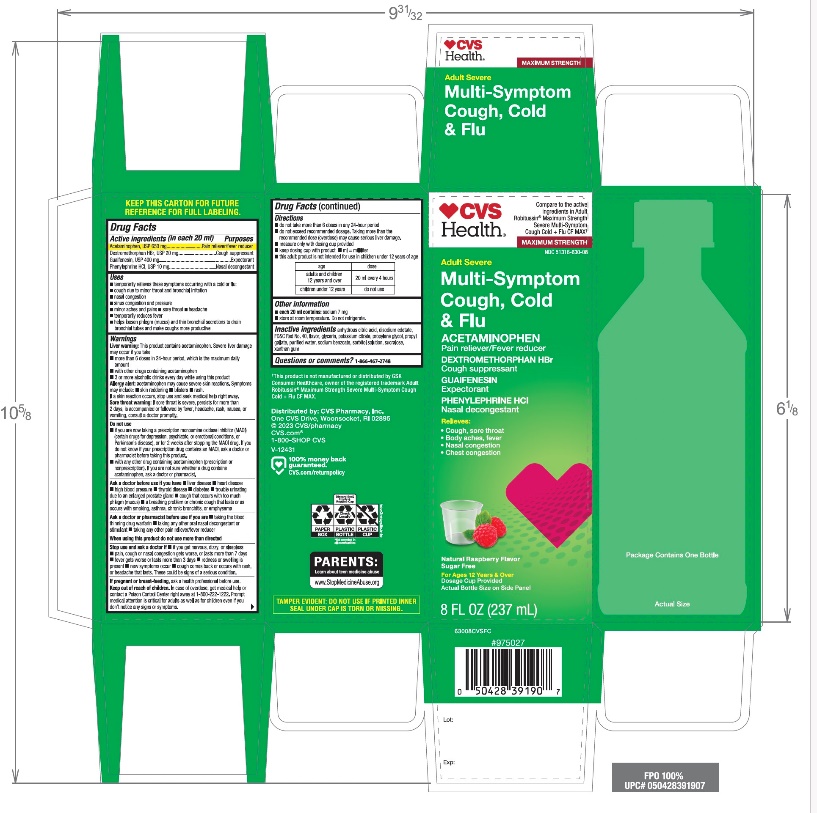 DRUG LABEL: CVS Severe Multi-Symptom Cough Cold Flu
NDC: 51316-630 | Form: LIQUID
Manufacturer: CVS PHARMACY
Category: otc | Type: HUMAN OTC DRUG LABEL
Date: 20251208

ACTIVE INGREDIENTS: ACETAMINOPHEN 650 mg/20 mL; DEXTROMETHORPHAN HYDROBROMIDE 20 mg/20 mL; GUAIFENESIN 400 mg/20 mL; PHENYLEPHRINE HYDROCHLORIDE 10 mg/20 mL
INACTIVE INGREDIENTS: ANHYDROUS CITRIC ACID; EDETATE DISODIUM; FD&C RED NO. 40; GLYCERIN; POTASSIUM CITRATE; PROPYLENE GLYCOL; PROPYL GALLATE; WATER; SODIUM BENZOATE; SORBITOL; SUCRALOSE; XANTHAN GUM

CVS Adult Severe Multi-Symptom Cough Cold+Flu Drug Facts

Active ingredients (in each 20 ml)

Acetaminophen, USP 650 mg

Dextromethorphan HBr, USP 20 mg

Guaifenesin, USP 400 mg

Phenylephrine HCl, USP 10 mg

Purposes

Pain reliever/Fever reducer

Cough suppressant

Expectorant

Nasal decongestant

Uses

- temporarily relieves these symptoms occurring with a cold or flu:
- cough due to minor throat and bronchial irritation
- nasal congestion
- sinus congestion and pressure
- minor aches and pains
- sore throat
- headache
- temporarily reduces fever
- helps loosen phlegm (mucus) and thin bronchial secretions to drain bronchial tubes and make coughs more productive

Warnings

Liver warning

This product contains acetaminophen. Severe liver damage may occur if you take

- more than 6 doses in any 24-hour period, which is the maximum daily amount
- with other drugs containing acetaminophen
- 3 or more alcoholic drinks every day while using this product

Allergy alert:acetaminophen may cause severe skin reactions. Symptoms may include:

- skin reddening
- blisters
- rash

If a skin reaction occurs, stop use and seek medical help right away.

Sore throat warning

If sore throat is severe, persists for more than 2 days, is accompanied or followed by fever, headache, rash, nausea, or vomiting, consult a doctor promptly.

Do not use

- if you are now taking a prescription monoamine oxidase inhibitor (MAOI) (certain drugs for depression, psychiatric, or emotional conditions, or Parkinson's disease), or for 2 weeks after stopping the MAOI drug. If you do not know if your prescription drug contains an MAOI, ask a doctor or pharmacist before taking this product.
- with any other drug containing acetaminophen (prescription or nonprescription). If you are not sure whether a drug contains acetaminophen, ask a doctor or pharmacist.

Ask a doctor before use if you have

- liver disease
- heart disease
- high blood pressure
- thyroid disease
- diabetes
- trouble urinating due to an enlarged prostate gland
- cough that occurs with too much phlegm (mucus)
- a breathing problem or chronic cough that lasts or as occurs with smoking, asthma, chronic bronchitis, or emphysema

Ask a doctor or pharmacist before use if you are

- taking the blood thinning drug warfarin
- taking any other oral nasal decongestant or stimulant
- taking any other pain reliever/fever reducer

When using this product do not use more than directed

Stop use and ask a doctor if

- you get nervous, dizzy, or sleepless
- pain, cough, or nasal congestion gets worse or lasts more than 7 days
- fever gets worse or lasts more than 3 days
- redness or swelling is present
- new symptoms occur
- cough comes back or occurs with rash or headache that lasts. These could be signs of a serious condition.

PREGNANCY OR BREAST FEEDING

If pregnant or breast-feeding,ask a health professional before use.

Keep out of reach of children.In case of overdose, get medical help or contact a Poison Control Center right away at 1-800-222-1222. Prompt medical attention is critical for adults as well as for children, even if you do not notice any signs or symptoms.

Directions

- do not take more than 6 doses in any 24-hour period
- do not exceed recommended dosage. Taking more than the recommended dose (overdose) may cause serious liver damage.
- measure only with dosing cup provided
- keep dosing cup with product
- ml = milliliter
- this adult product is not intended for use in children under 12 years of age

age | dose
adults and children 12 years and over | 20 ml every 4 hours
children under 12 years | do not use

Other information

- each 20 ml contains:sodium 7 mg
- store at room temperature. Do not refrigerate.

Inactive ingredients

anhydrous citric acid, edetate disodium, FD&C red no. 40, glycerin, flavors, potassium citrate, propylene glycol, propyl gallate, purified water, sodium benzoate, sorbitol solution, sucralose, xanthan gum

Questions or comments?

1-866-467-2748

Distributed by:

PRINCIPAL DISPLAY PANEL

Compare to the active ingredients in Adult Robitussin Maximum Strength SEVERE Multi-Symptom Cough Cold + Flu CF MAX*

NDC 51316-630-04

MAXIMUM STRENGTH

Adult

SEVERE
Multi-Symptom
Cough Cold + Flu

ACETAMINOPHEN (Pain Reliever/Fever Reducer)
Dextromethorphan HBr (Cough Suppressant)
Guaifenesin (Expectorant)
Phenylephrine HCl (Nasal Decongestant)

- Cough, Sore Throat
- Body Aches, Fever
- Nasal Congestion
- Chest Congestion

Sugar-Free

No Added Alcohol

Natural Raspberry Flavor

For Ages 12 & Over
8 FL OZ (237 ml)

*This product is not manufactured or distributed by GSK Consumer Healthcare, Owner o the registered trademark Adult Robitussin Maximum Strength SEVERE Multi-Symptom Cough Cold + Flu CF MAX.